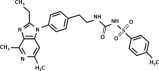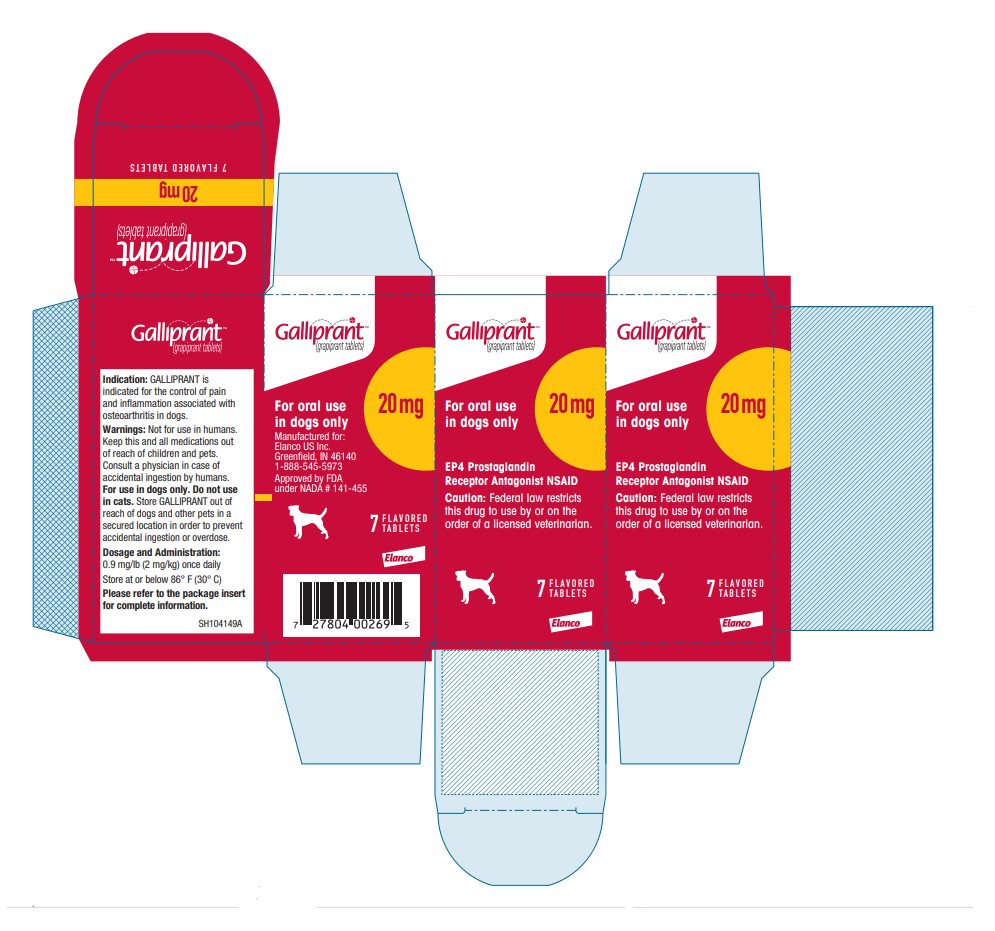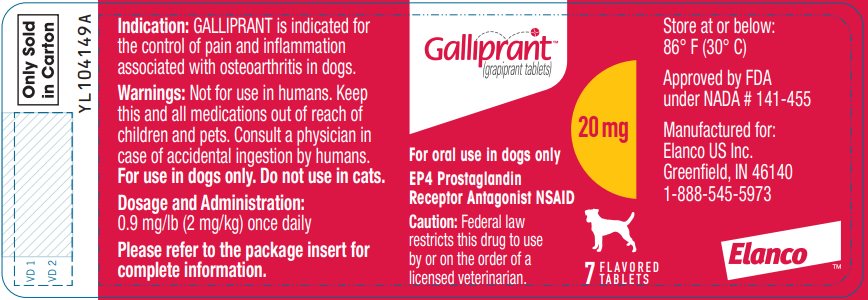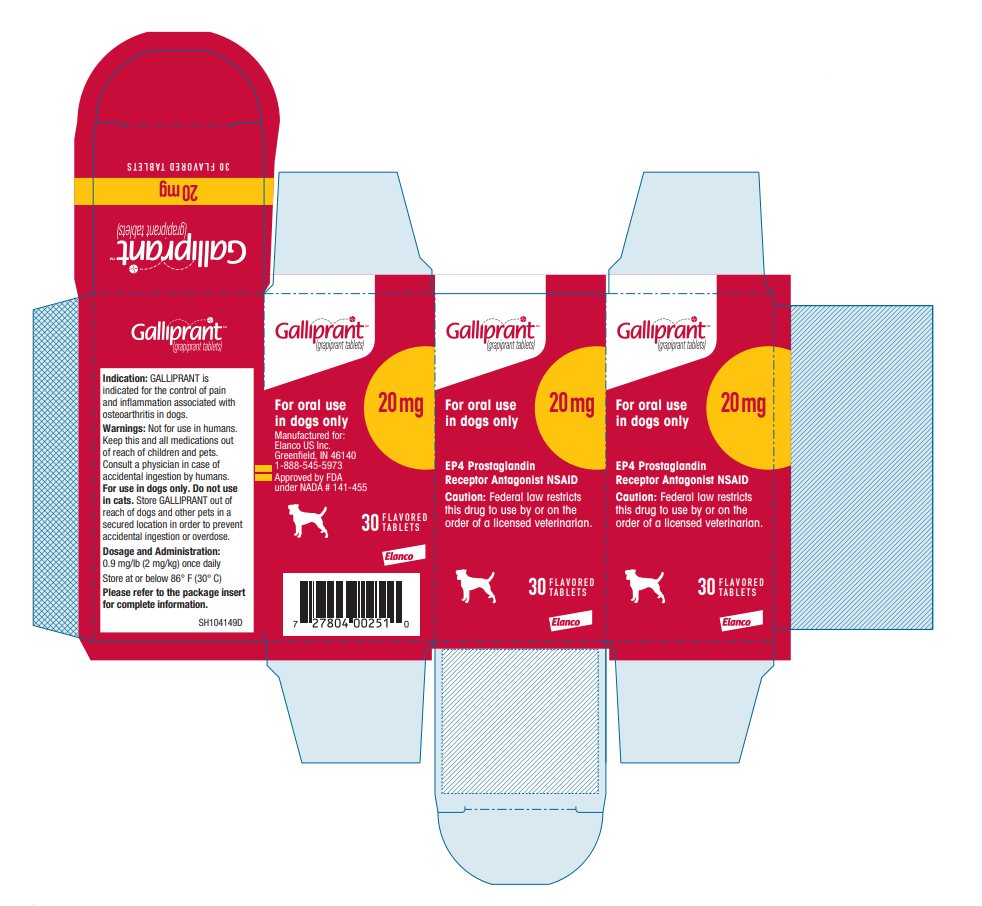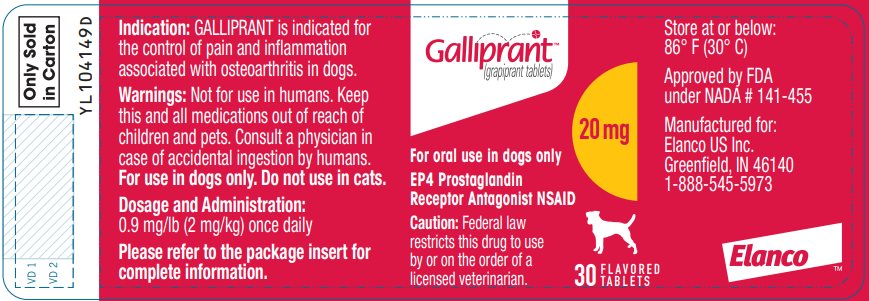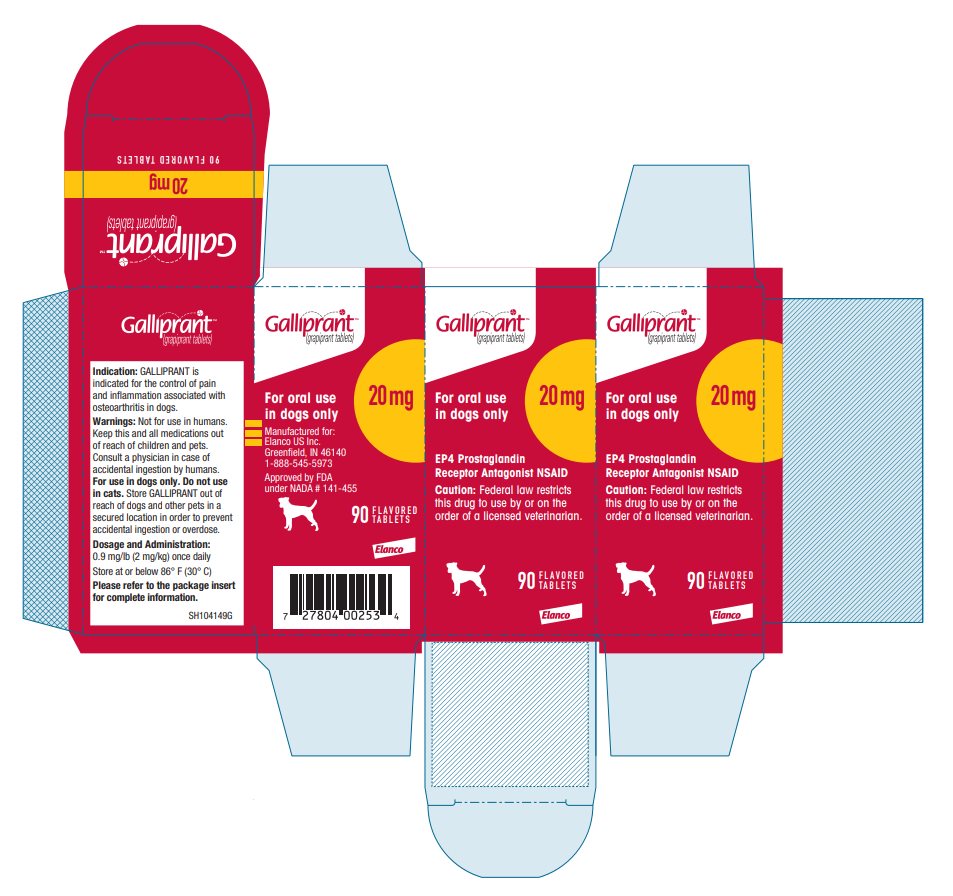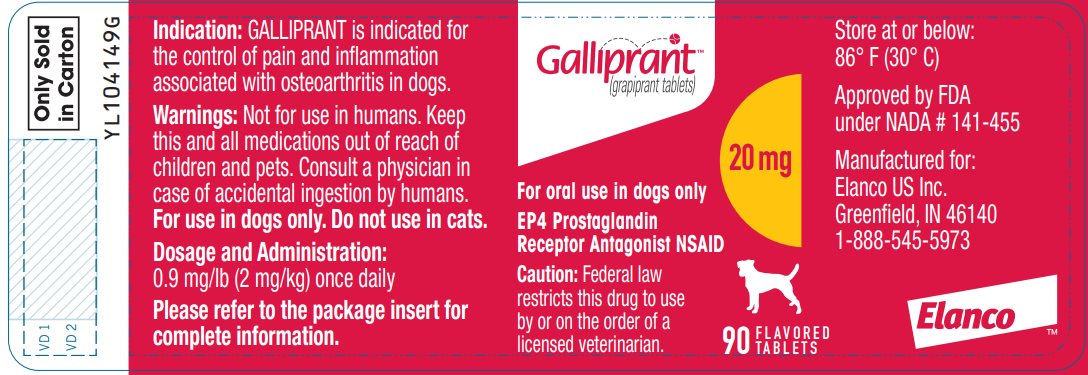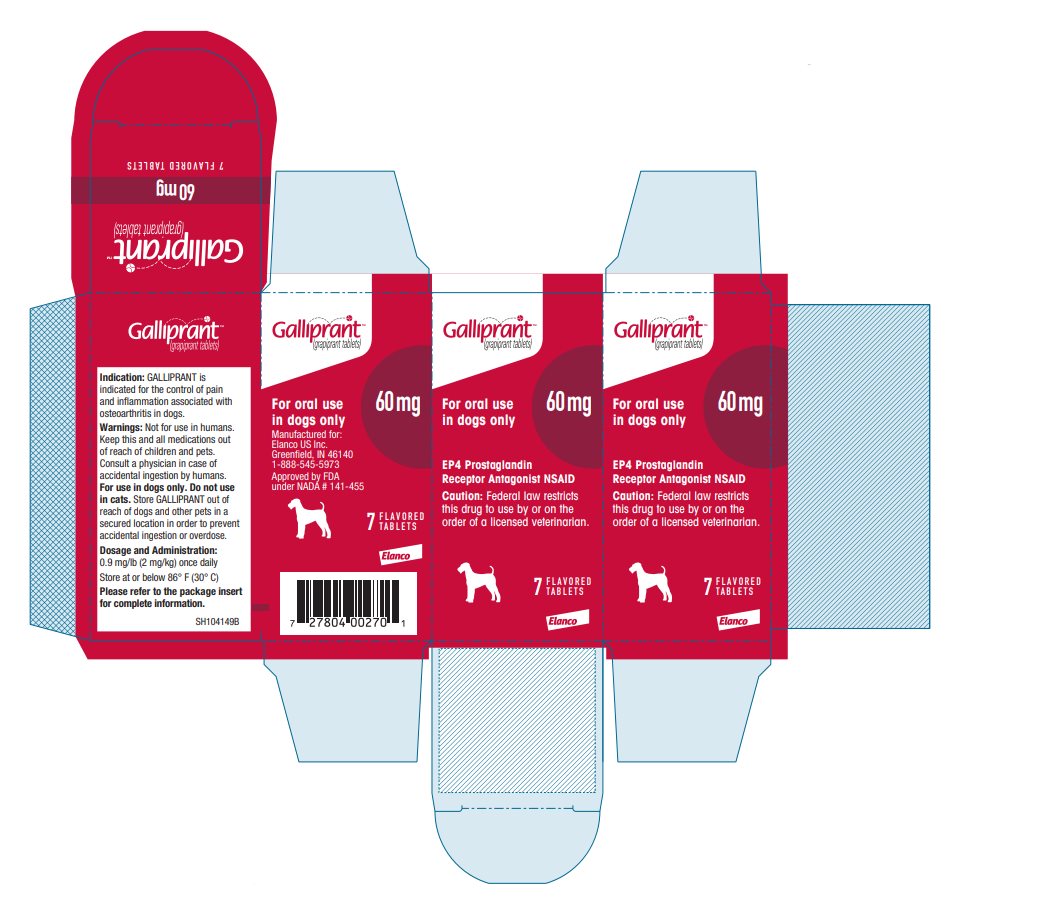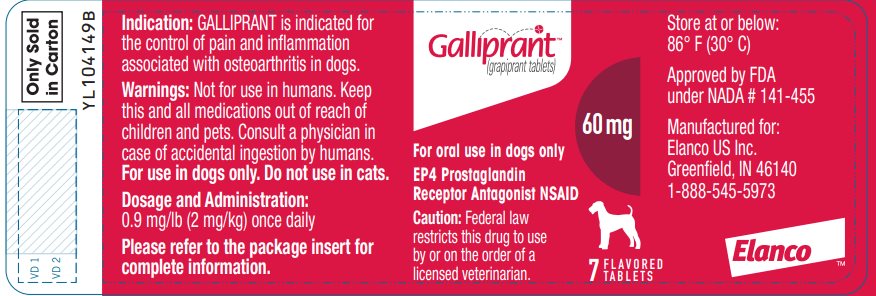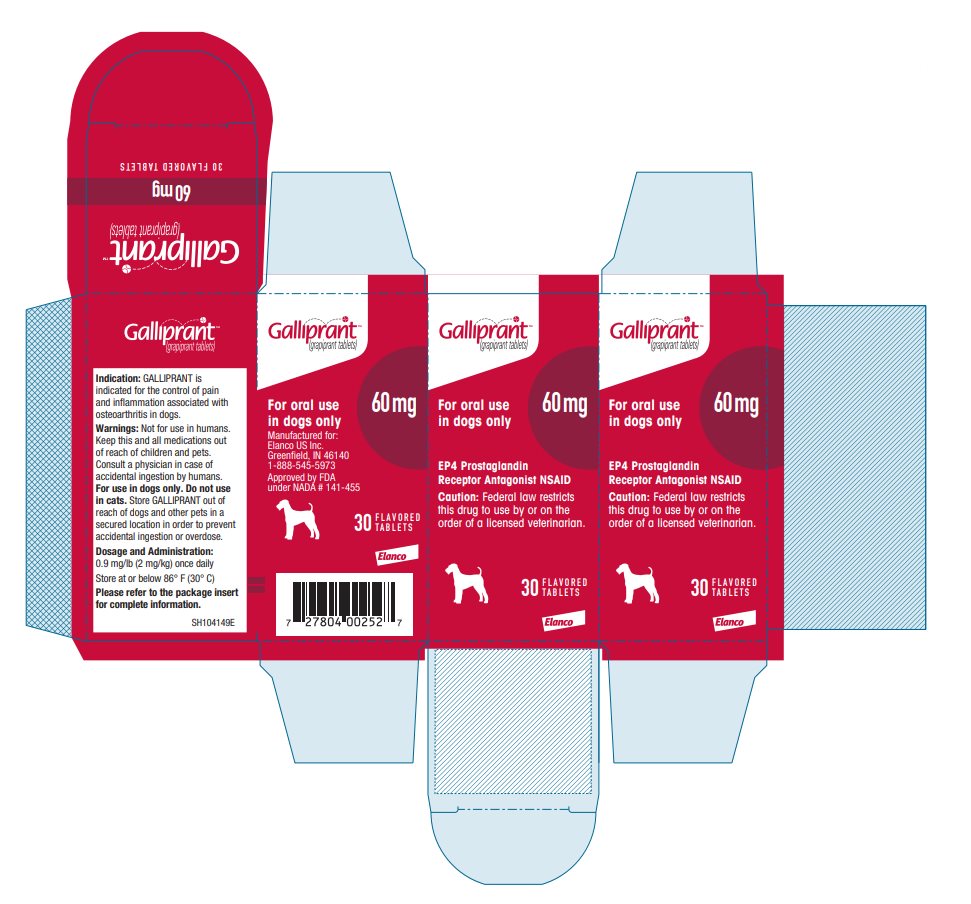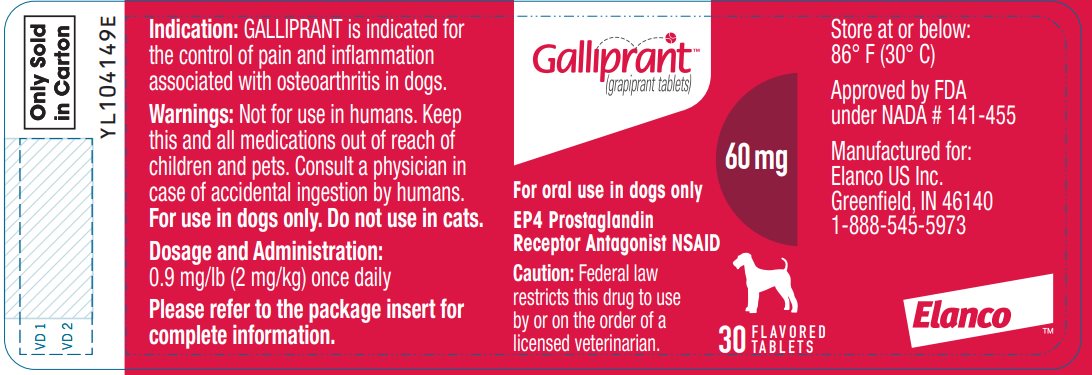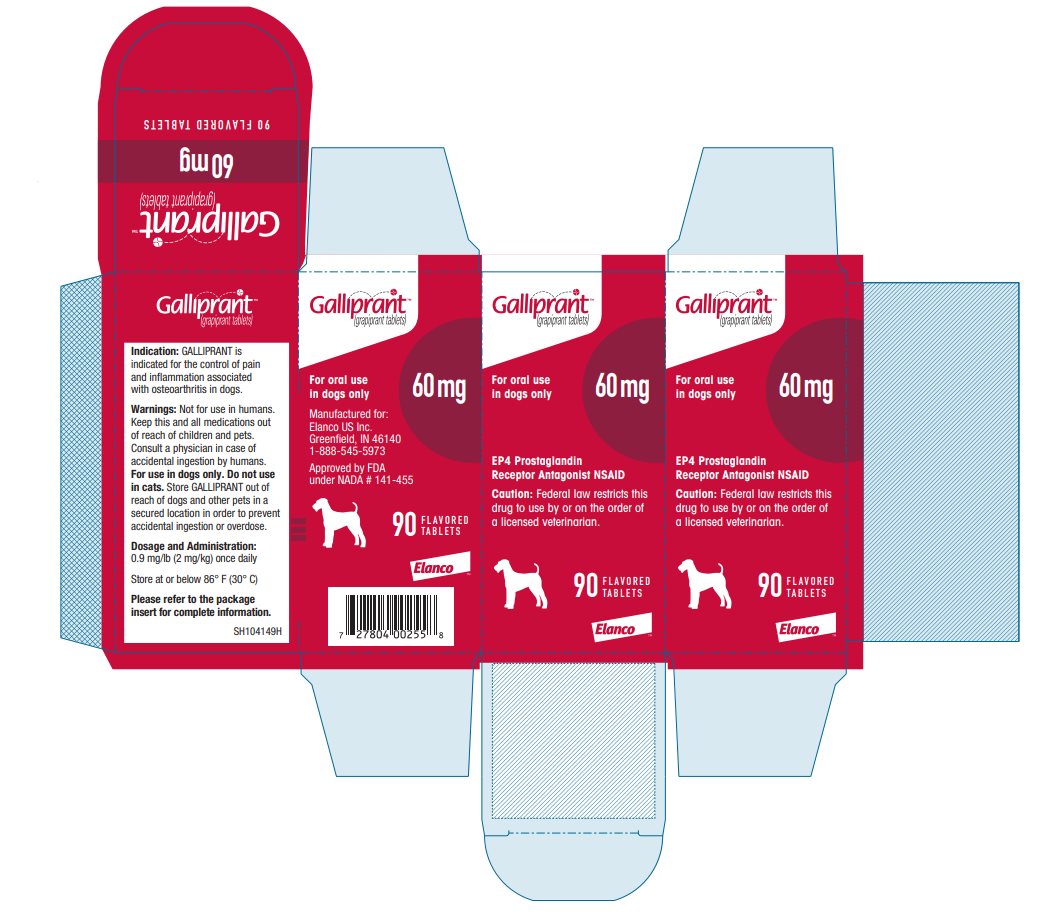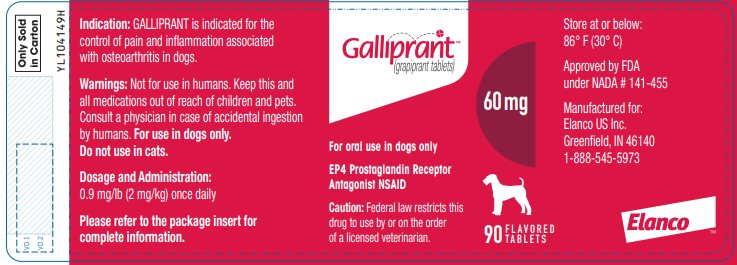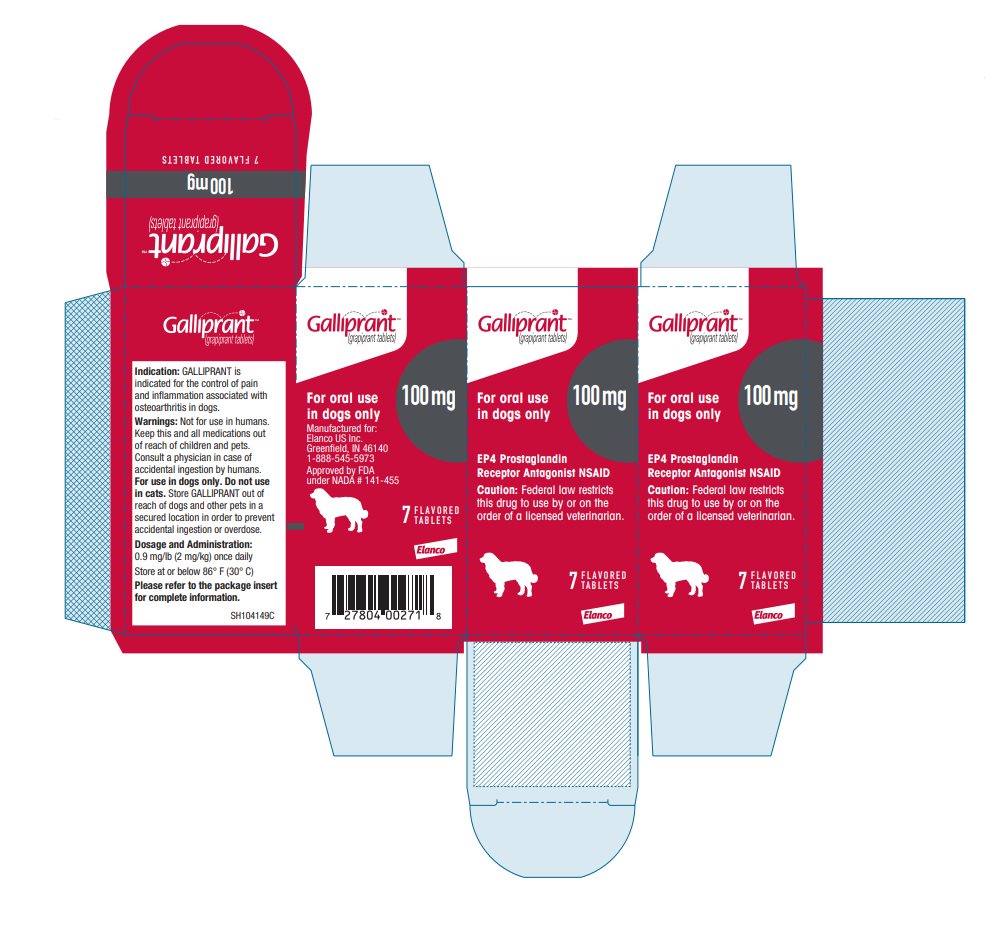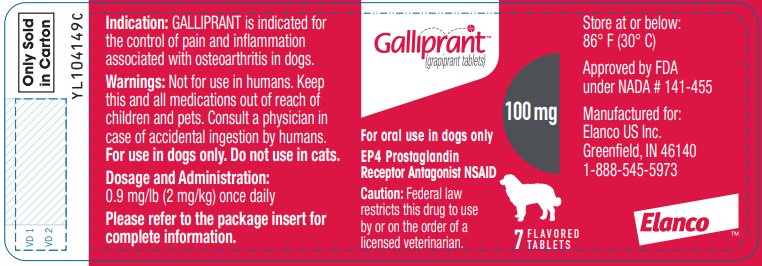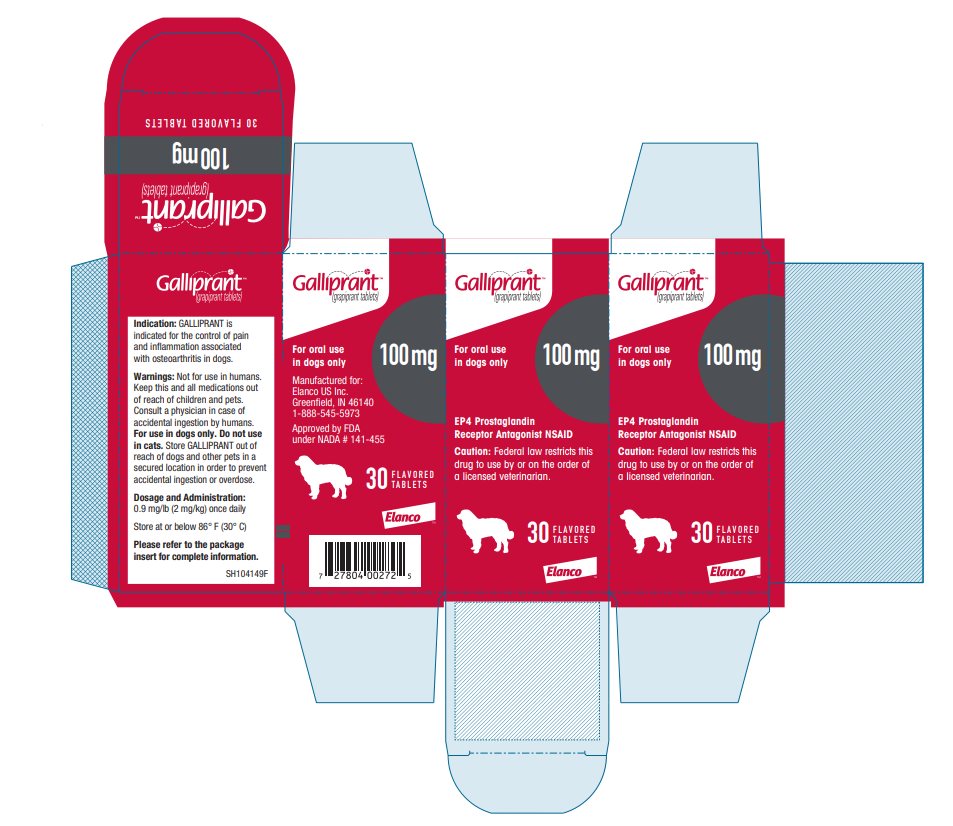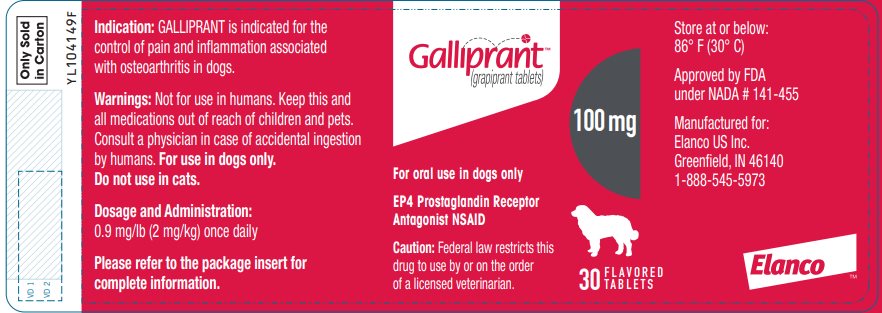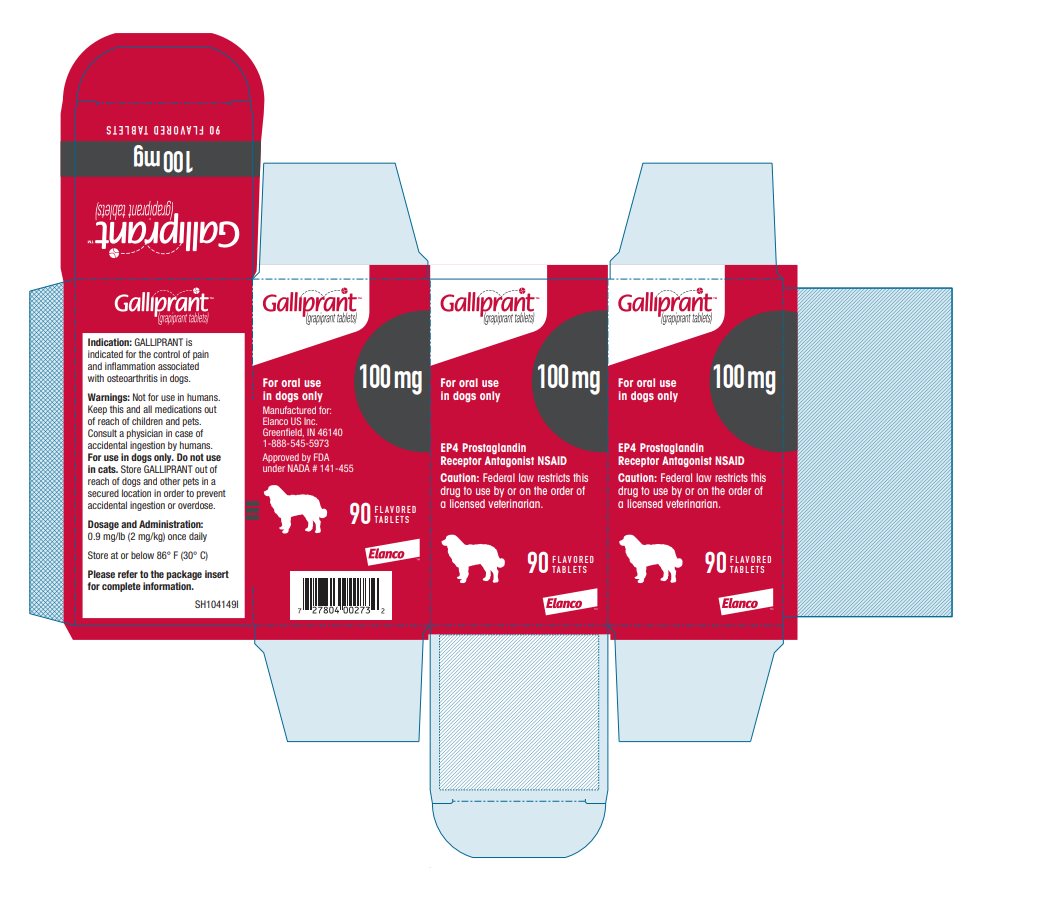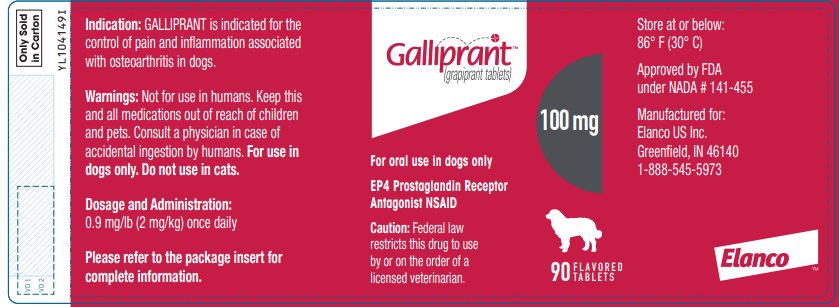 DRUG LABEL: Galliprant
NDC: 58198-5810 | Form: TABLET
Manufacturer: Elanco US Inc.
Category: animal | Type: PRESCRIPTION ANIMAL DRUG LABEL
Date: 20250811

ACTIVE INGREDIENTS: Grapiprant 20 mg/1 1

GalliprantTM

(grapiprant tablets)

For oral use in dogs only

20 mg, 60 mg and 100 mg flavored tablets

A prostaglandin E2 (PGE2) EP4 receptor antagonist; a non-cyclooxygenase inhibiting, non-steroidal anti-inflammatory drug

Caution:

Federal law restricts this drug to use by or on the order of a licensed veterinarian.

Description:

GALLIPRANT (grapiprant tablets) is a prostaglandin E2 (PGE2) EP4 receptor antagonist; a non-cyclooxygenase (COX) inhibiting, non-steroidal anti-inflammatory drug (NSAID) in the piprant class. GALLIPRANT is a flavored, oval, biconvex, beige to brown in color tablet debossed with a “G” that contains grapiprant and desiccated pork liver as the flavoring agent. The 20 mg and 60 mg tablets are scored. The 100 mg tablet is not scored.

The molecular weight of grapiprant is 491.61 Daltons. The empirical formula is C26H29N5O3S. Grapiprant is N-[[[2-[4-(2-Ethyl-4,6-dimethyl-1H-imidazo[4,5-c] pyridin-1-yl)phenyl]ethyl]amino]carbonyl]-4 methylbenzenesulfonamide.

The structural formula is:

Indication:

GALLIPRANT (grapiprant tablets) is indicated for the control of pain and inflammation associated with osteoarthritis in dogs.

Dosage and Administration:

Always provide “Information for Dog Owners” Sheet with prescription.

Carefully consider the potential benefits and risks of GALLIPRANT and other treatment options before deciding to use GALLIPRANT. Use the lowest effective dose for the shortest duration consistent with individual response.

The dose of GALLIPRANT (grapiprant tablets) is 0.9 mg/lb (2 mg/kg) once daily.

Only the 20 mg and 60 mg tablets of GALLIPRANT are scored.

The dosage should be calculated in half tablet increments.
Dogs less than 8 lbs. (3.6 kgs) cannot be accurately dosed.

Dosing Chart

Dose | Weight in pounds | Weight in kilograms | 20 mg tablet | 60 mg tablet | 100 mg tablet
0.9 mg/lb (2 mg/kg) once daily | 8-15 | 3.6-6.8 | 0.5
0.9 mg/lb (2 mg/kg) once daily | 15.1-30 | 6.9-13.6 | 1
0.9 mg/lb (2 mg/kg) once daily | 30.1-45 | 13.7-20.4 |  | 0.5
0.9 mg/lb (2 mg/kg) once daily | 45.1-75 | 20.5-34 |  | 1
0.9 mg/lb (2 mg/kg) once daily | 75.1-150 | 34.1-68 |  |  | 1

The 100 mg tablet is not scored and should not be broken in half.

Breaking the 100 mg tablet in half will not guarantee that half of the active ingredient is contained within each half of the tablet. For dogs larger than 150 lbs (68 kgs), use a combination of tablet and half tablets to achieve the appropriate dose.

Contraindications:

GALLIPRANT should not be used in dogs that have a hypersensitivity to grapiprant.

Warnings:

Not for use in humans. Keep this and all medications out of reach of children and pets. Consult a physician in case of accidental ingestion by humans. For use in dogs only. All dogs should undergo a thorough history and physical examination before the initiation of NSAID therapy. Appropriate laboratory tests to establish hematological and serum biochemical baseline data prior to and periodically during administration of any NSAID is recommended.

Owners should be advised to observe for signs of potential drug toxicity (see Adverse Reactions, Post-Approval Experience, and Animal Safety) and be given an “Information for Dog Owners” Sheet about GALLIPRANT.

Do not administer GALLIPRANT in conjunction with any other oral or injectable NSAID or corticosteroid.

Keep GALLIPRANT in a secure location out of reach of dogs, cats, and other animals to prevent accidental ingestion or overdose.

Precautions:

The safe use of GALLIPRANT has not been evaluated in dogs younger than 9 months of age and less than 8 lbs (3.6 kgs), dogs used for breeding, or in pregnant or lactating dogs.

Adverse reactions in dogs receiving GALLIPRANT may include vomiting, diarrhea, decreased appetite, mucoid, watery or bloody stools, and decreases in serum albumin and total protein (see Adverse Reactions and Post-Approval Experience).

If GALLIPRANT is used long term appropriate monitoring is recommended.

GALLIPRANT is a non-cyclooxygenase (COX) inhibiting non-steroidal anti-inflammatory drug (NSAID). As a class, NSAIDs may be associated with gastrointestinal, renal, and hepatic toxicity. Sensitivity to drug-associated adverse events varies with the individual patient. Dogs that have experienced adverse reactions from one NSAID may experience adverse reactions from another NSAID. Patients at greatest risk for adverse events are those that are dehydrated, on concomitant diuretic therapy, or those with existing renal, cardiovascular, and/or hepatic dysfunction.

Anesthetic drugs may affect renal perfusion; approach concomitant use of anesthetics and NSAIDs cautiously. Appropriate monitoring procedures (including ECG, blood pressure, and temperature regulation) should be employed during all surgical procedures. The use of parenteral fluids during surgery is recommended to decrease potential renal complications when using NSAIDs perioperatively.

If additional pain medication is needed after a daily dose of GALLIPRANT, a non-NSAID/non-corticosteroid class of analgesic may be necessary. Concurrent administration of potentially nephrotoxic drugs should be carefully approached and monitored. NSAIDs may inhibit the prostaglandins that maintain normal homeostatic function. GALLIPRANT blocks the activity of the specific prostaglandin E2 (PGE2). Such anti-prostaglandin effects may result in clinically significant disease in patients with underlying or pre-existing disease that has not been previously diagnosed. NSAIDs possess the potential to produce gastrointestinal ulceration and/or gastrointestinal perforation. Do not use GALLIPRANT concomitantly with other anti-inflammatory drugs, such as NSAIDs or corticosteroids. Consider appropriate washout times when switching from GALLIPRANT to another NSAID (or vice versa) or when switching from corticosteroid use to GALLIPRANT use.

The concomitant use of protein-bound drugs with GALLIPRANT has not been studied in dogs. Commonly used protein-bound drugs include cardiac, anticonvulsant and behavioral medications. The influence of concomitant drugs that may inhibit metabolism of GALLIPRANT has not been evaluated. Drug compatibility should be monitored in patients requiring adjunctive therapy.

The use of GALLIPRANT in dogs with cardiac disease has not been studied.

It is not known whether dogs with a history of hypersensitivity to sulfonamide drugs will exhibit hypersensitivity to GALLIPRANT. GALLIPRANT is a methylbenzenesulfonamide.

Adverse Reactions:

In a controlled field study, 285 dogs were evaluated for safety when given either GALLIPRANT or a vehicle control (tablet minus grapiprant) at a dose of 2 mg/kg (0.9 mg/lb) once daily for 28 days. GALLIPRANT-treated dogs ranged in age from 2 to 16.75 years. The following adverse reactions were observed:

Table 1. Adverse reactions reported in the field study.
Adverse reaction* | GALLIPRANT (grapiprant tablets) N = 141 | Vehicle control (tablets minus grapiprant) N = 144
Vomiting | 24 | 9
Diarrhea, soft stool | 17 | 13
Anorexia, inappetence | 9 | 7
Lethargy | 6 | 2
Buccal ulcer | 1 | 0
Immune mediated hemolytic anemia | 1 | 0
*Dogs may have experienced more than one type or occurrence during the study.

GALLIPRANT was used safely during the field studies with other concurrent therapies, including antibiotics, parasiticides and vaccinations.

Post-Approval Experience (2024)

The following adverse events are based on post-approval adverse drug experience reporting for GALLIPRANT. Not all adverse events are reported to FDA/CVM. It is not always possible to reliably estimate the adverse event frequency or establish a causal relationship to product exposure using these data.

The following adverse events in dogs are categorized in order of decreasing reporting frequency by body system and in decreasing order of reporting frequency within each body system:

GI: diarrhea (with or without blood), vomiting (with or without blood), elevated pancreatic enzymes/pancreatitis, melena, bloody stool, hypoalbuminemia, abdominal pain, gastrointestinal ulcer.
General: anorexia, lethargy, weight loss, panting, hyperactivity.
Hepatic: elevated liver enzymes.
Renal/Urinary: increased BUN or creatinine, polydipsia, urinary incontinence/inappropriate urination, polyuria, renal failure.
Neurologic: ataxia, seizures.
Hematologic: anemia, thrombocytopenia.
Dermatologic/Immunologic: pruritus, allergic reactions (including facial edema and hives), immune mediated hemolytic anemia.

In some cases, death (including euthanasia) has been reported as an outcome of the adverse events listed above.

Contact Information:

To report suspected adverse drug experiences and/or obtain a copy of the Safety Data Sheet (SDS) or for technical assistance, contact Elanco US Inc. at 1-888-545-5973.

For additional information about adverse drug experience reporting for animal drugs, contact FDA at 1-888-FDA-VETS or http://www.fda.gov/reportanimalae.

Information for Dog Owners:

Owners should be advised of the potential for adverse reactions and be informed of the clinical signs associated with drug intolerance. Adverse reactions may include diarrhea, vomiting, decreased appetite, dark or tarry stools, increased water consumption, increased urination, pale gums due to anemia, jaundice (yellowing of gums, skin or white of the eye), lethargy, incoordination, seizures, and behavioral changes such as depression or restlessness. Serious adverse reactions associated with this drug class can occur without warning and, in some cases, result in death (see Adverse Reactions and Post-Approval Experience).

Owners should be advised to discontinue GALLIPRANT therapy and contact their veterinarian immediately if signs of intolerance are observed. The vast majority of patients with drug related adverse reactions have recovered when the signs are recognized, the drug is withdrawn, and veterinary care, if appropriate, is initiated. Owners should be advised of the importance of periodic follow up for all dogs during administration of any NSAID.

Clinical Pharmacology:

Grapiprant is a prostaglandin E2 (PGE2) EP4 receptor antagonist; a non- cyclooxygenase inhibiting, non-steroidal, anti-inflammatory drug. Grapiprant has a canine EP4 receptor binding affinity (Ki) of 24 nM.

Prostaglandins have a wide variety of physiologic effects. Prostaglandin E2 (PGE2) is a prostanoid that exerts its effects via four receptors, EP1, EP2, EP3, and EP4. PGE2 is involved in mediating inflammatory pain, vasodilation, increasing vascular permeability; as well as gastrointestinal homeostasis, renal function and reproductive functions. The EP4 receptor is important in mediating pain and inflammation as it is the primary mediator of the PGE2-elicited sensitization of sensory neurons^1 and PGE2-elicited inflammation.^2 Grapiprant blocks PGE2-elicited pain and inflammation by antagonizing the EP4 receptor.

The EP4 receptor, along with the EP1, EP2 and EP3 receptors, is involved in PGE2 mediated effects on gastrointestinal homeostasis and renal function. PGE2 effects mediated solely by the EP4 receptor are stimulation of mucus secretion in the stomach and large intestine, stimulation of acid secretion in the stomach, inhibition of small intestine motility and inhibition of cytokine expression in the large intestine.^3 While PGE2 gastroprotective action is mediated by EP1, the healing- promoting action of PGE2 in the stomach is mediated by the EP4 receptor.^4 In the kidney, the PGE2 antinatiuretic effect is mediated by the EP4 receptor.^5

EP4 receptors are abundantly expressed in the heart of dogs,^6 the clinical relevance of which is unknown. The EP4 receptor is not involved in generation of pyrexia.

Grapiprant is not a potential inhibitor of CYP1A2, CYP2C9, CYP2C19, CYP2D6, and CYP3A4 mediated metabolism pathways. Grapiprant is a substrate of P-glycoprotein transport. In vitro metabolism with dog liver microsomes identified two oxidative metabolites, M3 (hydroxyl) and M5 (N-dealkylation).

The pharmacokinetic characterization of grapiprant following oral administration of GALLIPRANT tablets to healthy Beagles is provided in the table below.

Table 2. Mean (±SD) Plasma Pharmacokinetic Parameters for Grapiprant in Beagles after single oral dose of GALLIPRANT tablet formulation
Study | Study 1^1 | Study 1^1 | Study 2^2 | Study 2^2
PK Parameter | 2 mg/kg (n = 10) (Fasted) | 2 mg/kg (n = 10) (Fed) | 6 mg/kg (n = 8) (Fasted) | 50 mg/kg (n = 8) (Fasted)
Tmax^3 (hr) | 1.0 (0.5 – 1.03) | 1.0 (0.5 – 8.07) | 1.0 (1.0 – 2.0) | 2.0 (1.0 – 4.0)
Cmax (ng/mL) | 1210 (341) | 278 (179) | 5720 (3220) | 98500 (13100)
AUC(0-inf) (ng*hr/mL) | 2790 (982) | 1200 (523) | 17800 (5520) | 414000 (73700)
T1/2 (hr) | 4.60 (4.19) | 5.67 (3.27) | 5.01 (1.95) | 5.21 (1.66)
Fed/Fasted Relative Bioavailability Geometric Mean Ratio of AUC (90% Confidence Limits) | 0.37 (0.28 – 0.46) |  | NA
^1Study 1 was a food effect determination study.
^2Study 2 was a PK bridging study conducted using 60 mg GALLIPRANT tablets at 6 mg/kg dose and 5 X 100 mg GALLIPRANT tablets at 50 mg/kg dose.
^3Median (Range)

Grapiprant is absorbed rapidly following an oral dose of the GALLIPRANT; with Cmax values achieved within approximately 2 hr post-dose (Tmax). Intake of the tablet with food significantly reduces the oral bioavailability, with mean Cmax and AUC grapiprant values reduced 4-fold and 2-fold, respectively. The systemic grapiprant exposure increases in a greater than dose proportional manner.

The mean terminal elimination half-life (T1/2) ranges between 4.60 to 5.67 hr. Following once daily dosing, negligible drug accumulation in the blood is anticipated. Following an oral dose of radiolabeled grapiprant to dogs, the majority of the dose was excreted within the first 72 hr (84%) and approximately 88.7% of the dose was excreted in 192 hr. In a bile duct cannulated dog study, approximately 55.6%, 15.1% and 19.1% of the dose was excreted in bile, urine and feces, respectively, suggesting the high oral bioavailability of grapiprant in dogs (> 70%). Four metabolites were identified; two hydroxylated metabolites, one N-deamination metabolite (major metabolite urine (3.4%) and feces (7.2%)) and one N-oxidation metabolite. Metabolite activity is not known. Plasma protein binding of grapiprant was ~95%.

Effectiveness:

Two hundred and eighty five (285) client-owned dogs were enrolled in the study and evaluated for field safety. GALLIPRANT-treated dogs ranging in age from 2 to 16.75 years and weighing between 4.1 and 59.6 kgs (9 – 131 lbs) with radiographic and clinical signs of osteoarthritis were enrolled in a placebo-controlled, masked field study. Dogs had a 7-day washout from NSAID or other current OA therapy. Two hundred and sixty two (262) of the 285 dogs were included in the effectiveness evaluation. Dogs were assessed for improvements in pain and function by the owners using the Canine Brief Pain Inventory (CBPI) scoring system.^7 A statistically significant difference in the proportion of treatment successes in the GALLIPRANT group (63/131 or 48.1%) was observed compared to the vehicle control group (41/131 or 31.3%). GALLIPRANT demonstrated statistically significant differences in owner assessed pain and function. The results of the field study demonstrate that GALLIPRANT, administered at 2 mg/kg (0.9 mg/pound) once daily for 28 days, was effective for the control of pain and inflammation associated with osteoarthritis.

Animal Safety:

In a 9-month toxicity study, grapiprant in a methylcellulose suspension was administered by oral gavage once daily to healthy Beagles at doses of 1, 6, and 50 mg/kg/day. Based on a relative bioavailability study comparing grapiprant in methylcellulose suspension to GALLIPRANT tablets, the corresponding equivalent doses were 0.75 mg/kg (0.12X – 0.25X), 4.44 mg/kg (0.72X – 1.48X) and 30.47 mg/kg (4.88X – 10.16X) of the GALLIPRANT tablets. Four animals/sex were used in each dose group and 2 additional animals/sex were used in the 50 mg/kg dose group to evaluate recovery after drug cessation. Vomiting and soft-formed or mucus stool were observed in all groups, including controls, with higher incidence in grapiprant-treated dogs. Decreases in serum albumin and total protein were seen with increasing doses of grapiprant. Hypoalbuminemia and hypoproteinemia were reversible when treatment was discontinued. Three treated dogs and one control dog had elevated alkaline phosphatase values. One animal in the 50 mg/kg group (equivalent to 30.47 mg/kg of tablet formulation) had mild regeneration of the mucosal epithelium of the ileum.

In a field study conducted in 366 client-owned dogs to evaluate GALLIPRANT at doses of 2 mg/kg once daily, 5 mg/kg once daily, 4 mg/kg twice daily, or placebo twice daily, the most common adverse reactions related to treatment were diarrhea, vomiting and inappetence. Changes in clinical pathology included concurrent elevations of alkaline phosphatase and alanine aminotransferase values on Day 28, and dose-dependent decreases in total protein values. There was no clinical impact related to these clinical pathology changes.

Storage Conditions:

Store at or below 86° F (30° C)

How Supplied:

20 mg, 60 mg and 100 mg flavored tablets in 7, 30 and 90 count bottles

Approved by FDA under NADA # 141-455

Manufactured for: Elanco US Inc. Greenfield, IN 46140

References:

1. Nakao, K., Murase, A., et al. CJ-023,423, a novel, potent and selective prostaglandin EP4 receptor antagonist with antihyperalgesic properties. The Journal of Pharmacology and Experimental Therapeutics. 2007; 322(2), 686-694.
2. Murase, A., Okumura, T., et al. Effect of prostanoid EP4 receptor antagonist, CJ-042,794, in rat models of pain and inflammation. European Journal of Pharmacology. 2008; 580(1-2), 116-121.
3. Takeuchi, K., S. Kato, et al. Prostaglandin EP receptors involved in modulating gastrointestinal mucosal integrity. Journal of Pharmacological Sciences. 2010; 114(3): 248-261.
4. Hatazawa R, Tanaka A, Tanigami M, et al. Cyclooxygenase-2/prostaglandin E2 accelerates the healing of gastric ulcers via EP4 receptors. American Journal of Physiology-Gastrointestinal and Liver Physiology. 2007; 293: G788-G797.
5. Nasrallah R, Hassouneh R, and Hebert R. Chronic kidney disease: targeting prostaglandin E2 receptors. American Journal of Physiology Renal Physiology. 2014; 307: F242-250.
6. Castleberry TA, Lu B, et al. Molecular cloning and functional characterization of the canine prostaglandin E2 receptor EP4 subtype. Prostaglandins and Other Lipid Mediators. 2001; 65: 167-187.
7. http://www.vet.upenn.edu/docs/default-source/ VCIC/canine-bpi_userguide.pdf?sfvrsn=0

Galliprant, Elanco and the diagonal bar logo are trademarks of Elanco or its affiliates.
© 2024 Elanco or its affiliates

October 2024

PA104149X

ElancoTM

INFORMATION FOR OWNERS/CAREGIVERS

GalliprantTM
(grapiprant tablets)

For oral use in dogs only
Information for Dog Owners

GALLIPRANT is indicated for the control of pain and inflammation due to osteoarthritis.

This sheet contains important information about GALLIPRANT. You should read this information before starting your dog on GALLIPRANT and review it each time the prescription is refilled. This information provides a summary and does not take the place of the instructions from your veterinarian. Talk to your veterinarian if you do not understand any of this information or you want more information about GALLIPRANT.

What is GALLIPRANT?

GALLIPRANT is an EP4 prostaglandin receptor antagonist non-steroidal, anti-inflammatory drug (NSAID). As an anti-inflammatory, GALLIPRANT is indicated for the control of pain and inflammation associated with osteoarthritis in dogs.

Control of pain and inflammation may vary from dog to dog. Consult your veterinarian if your dog appears to be uncomfortable. GALLIPRANT may need to be given for an extended period of time. Use the lowest dose to provide adequate pain control. Always consult with your veterinarian before altering the dose.

It is important to periodically discuss your dog’s response to GALLIPRANT with your veterinarian. Your veterinarian will discuss appropriate monitoring while your dog is on GALLIPRANT.

Your dog should not take GALLIPRANT if:

- Your dog is presently taking aspirin, other NSAIDs (non-steroidal anti-inflammatory drugs such as carprofen or meloxicam) or corticosteroids (such as prednisone) unless directed by your veterinarian.
- Your dog has had an allergic reaction (such as hives, facial swelling, or itchy skin) to GALLIPRANT.
- Your dog has bloody stool or vomit.
- Your dog has a pre-existing kidney or liver condition.
- Your dog has any condition predisposing to dehydration.
- Your dog is anorexic (loss of appetite).
- Your dog is under 8 pounds in body weight.

GALLIPRANT should only be given to dogs.
Do not use in cats.

People should not take GALLIPRANT. Keep GALLIPRANT and all medications out of reach of children. Consult a physician if you accidentally take GALLIPRANT.

Keep GALLIPRANT in a secure location out of reach of dogs, cats, and other animals to prevent accidental ingestion or overdose.

Tell your veterinarian about:

- Any side effects your dog has experienced from GALLIPRANT or other NSAIDs. Dogs that have experienced side effects from one NSAID may experience adverse reactions from another NSAID.
- Any digestive issues (bloody or mucoid stool, vomiting, diarrhea, or decreased appetite) your dog has had.
- If your dog has no appetite or a decreased appetite.
- Any heart, kidney, or liver disease your dog has had.
- Any other medical problems or allergies that your dog has now or has had in the past.
- All medications that you are giving your dog or plan to give your dog, including those you can get without a prescription and any dietary supplements.
- If you plan to breed your dog, or if your dog is pregnant or nursing.

Talk to your veterinarian about:

- The signs of osteoarthritis you have observed (for example, limping or stiffness).
- What tests should be done prior to administering GALLIPRANT.
- How often your dog may need to be examined by your veterinarian.
- The risks and benefits of using GALLIPRANT.

What are the possible side effects that may occur in my dog during therapy with GALLIPRANT?

GALLIPRANT may cause some side effects in individual dogs. Serious side effects associated with this drug can occur with or without warning and, in some cases, result in death. The most common side effects associated with GALLIPRANT therapy involve the digestive tract (diarrhea, soft, mucoid stools, vomiting, and decreased appetite). Liver and kidney problems have also been reported.

Look for the following side effects that may indicate that your dog is having a problem with GALLIPRANT or may have another medical problem:

- Change in bowel movements such as diarrhea, soft mucoid stool, or change in stool color (black, tarry, or bloody stool).
- Vomiting.
- Decrease in appetite.
- Change in behavior, such as depression or restlessness.
- Incoordination or seizures.
- Change in drinking or urination.
- Yellowing of gums, skin, or whites of the eyes (jaundice).

It is important to stop the medication and contact your veterinarian immediately if you think your dog may have a medical problem or side effect while on GALLIPRANT.

If you have additional questions about possible side effects, talk with your veterinarian or call Elanco US Inc. at 1-888-545-5973. For additional information about adverse drug experience reporting for animal drugs, contact FDA at 1-888-FDA-VETS or http://www.fda.gov/reportanimalae.

Can GALLIPRANT be given with other medications?

GALLIPRANT should not be given with aspirin, other non-steroidal anti-inflammatory drugs (such as carprofen or meloxicam) or corticosteroids (such as prednisone).

Tell your veterinarian about all medications that you have given your dog in the past and any medications that you are planning to give with GALLIPRANT. This should include any medications that you can get without a prescription and any dietary supplements. Your veterinarian may want to evaluate the potential for any drug interactions and to assure drug compatibility.

What can I do in case my dog eats more than the prescribed amount of GALLIPRANT?

Contact your veterinarian immediately if your dog eats more than the prescribed amount of GALLIPRANT.

What else should I know about GALLIPRANT?

Keep GALLIPRANT in a secure location out of reach of dogs, cats, and other animals to prevent accidental ingestion or overdose.

If you have any questions or concerns about GALLIPRANT or osteoarthritis, talk to your veterinarian. GALLIPRANT should only be given to the dog for which it was prescribed. It should be given to your dog only for the condition for which it was prescribed, at the prescribed dose, as directed by your veterinarian. Your veterinarian will determine if your dog is responding as expected and if your dog should continue receiving GALLIPRANT.

Galliprant, Elanco and the diagonal bar logo are trademarks of Elanco or its affiliates.

October 2024

PA104149X

ElancoTM

Principal Display Panel - Galliprant 20 mg 7 Tablets Carton Label

GalliprantTM
(grapiprant tablets)

20 mg

For oral use
in dogs only

EP4 Prostaglandin
Receptor Antagonist NSAID

Caution: Federal law restricts
this drug to use by or on the
order of a licensed veterinarian.

7
FLAVORED
TABLETS

Elanco

Principal Display Panel - Galliprant 20 mg 7 Tablets Bottle Label

GalliprantTM
(grapiprant tablets)

20 mg

For oral use in dogs only

EP4 Prostaglandin
Receptor Antagonist NSAID

Caution: Federal law
restricts this drug to use
by or on the order of a
licensed veterinarian.

7
FLAVORED
TABLETS

Principal Display Panel - Galliprant 20 mg 30 Tablets Carton Label

GalliprantTM
(grapiprant tablets)

20 mg

For oral use
in dogs only

EP4 Prostaglandin
Receptor Antagonist NSAID

Caution: Federal law restricts
this drug to use by or on the
order of a licensed veterinarian.

30
FLAVORED
TABLETS

Elanco

Principal Display Panel - Galliprant 20 mg 30 Tablets Bottle Label

GalliprantTM
(grapiprant tablets)

20 mg

For oral use in dogs only

EP4 Prostaglandin
Receptor Antagonist NSAID

Caution: Federal law
restricts this drug to use
by or on the order of a
licensed veterinarian.

30
FLAVORED
TABLETS

Principal Display Panel - Galliprant 20 mg 90 Tablets Carton Label

GalliprantTM
(grapiprant tablets)

20 mg

For oral use
in dogs only

EP4 Prostaglandin
Receptor Antagonist NSAID

Caution: Federal law restricts
this drug to use by or on the
order of a licensed veterinarian.

90
FLAVORED
TABLETS

Elanco

Principal Display Panel - Galliprant 20 mg 90 Tablets Bottle Label

GalliprantTM
(grapiprant tablets)

20 mg

For oral use in dogs only

EP4 Prostaglandin
Receptor Antagonist NSAID

Caution: Federal law
restricts this drug to use
by or on the order of a
licensed veterinarian.

90
FLAVORED
TABLETS

Principal Display Panel - Galliprant 60 mg 7 Tablets Carton Label

GalliprantTM
(grapiprant tablets)

60 mg

For oral use
in dogs only

EP4 Prostaglandin
Receptor Antagonist NSAID

Caution: Federal law restricts
this drug to use by or on the
order of a licensed veterinarian.

7
FLAVORED
TABLETS

Elanco

Principal Display Panel - Galliprant 60 mg 7 Tablets Bottle Label

GalliprantTM
(grapiprant tablets)

60 mg

For oral use in dogs only

EP4 Prostaglandin
Receptor Antagonist NSAID

Caution: Federal law
restricts this drug to use
by or on the order of a
licensed veterinarian.

7
FLAVORED
TABLETS

Principal Display Panel - Galliprant 60 mg 30 Tablets Carton Label

GalliprantTM
(grapiprant tablets)

60 mg

For oral use
in dogs only

EP4 Prostaglandin
Receptor Antagonist NSAID

Caution: Federal law restricts
this drug to use by or on the
order of a licensed veterinarian.

30
FLAVORED
TABLETS

Elanco

Principal Display Panel - Galliprant 60 mg 30 Tablets Bottle Label

GalliprantTM
(grapiprant tablets)

60 mg

For oral use in dogs only

EP4 Prostaglandin
Receptor Antagonist NSAID

Caution: Federal law
restricts this drug to use
by or on the order of a
licensed veterinarian.

30
FLAVORED
TABLETS

Principal Display Panel - Galliprant 60 mg 90 Tablets Carton Label

GalliprantTM
(grapiprant tablets)

60 mg

For oral use
in dogs only

EP4 Prostaglandin
Receptor Antagonist NSAID

Caution: Federal law restricts this
drug to use by or on the order of
a licensed veterinarian.

90
FLAVORED
TABLETS

Elanco

Principal Display Panel - Galliprant 60 mg 90 Tablets Bottle Label

GalliprantTM
(grapiprant tablets)

60 mg

For oral use in dogs only

EP4 Prostaglandin Receptor
Antagonist NSAID

Caution: Federal law restricts this
drug to use by or on the order
of a licensed veterinarian.

90
FLAVORED
TABLETS

Principal Display Panel - Galliprant 100 mg 7 Tablets Carton Label

GalliprantTM
(grapiprant tablets)

100 mg

For oral use
in dogs only

EP4 Prostaglandin
Receptor Antagonist NSAID

Caution: Federal law restricts
this drug to use by or on the
order of a licensed veterinarian.

7
FLAVORED
TABLETS

Elanco

Principal Display Panel - Galliprant 100 mg 7 Tablets Bottle Label

GalliprantTM
(grapiprant tablets)

100 mg

For oral use in dogs only

EP4 Prostaglandin
Receptor Antagonist NSAID

Caution: Federal law
restricts this drug to use
by or on the order of a
licensed veterinarian.

7
FLAVORED
TABLETS

Principal Display Panel - Galliprant 100 mg 30 Tablets Carton Label

GalliprantTM
(grapiprant tablets)

100 mg

For oral use
in dogs only

EP4 Prostaglandin
Receptor Antagonist NSAID

Caution: Federal law restricts this
drug to use by or on the order of
a licensed veterinarian.

30
FLAVORED
TABLETS

Elanco

Principal Display Panel - Galliprant 100 mg 30 Tablets Bottle Label

GalliprantTM
(grapiprant tablets)

100 mg

For oral use in dogs only

EP4 Prostaglandin Receptor
Antagonist NSAID

Caution: Federal law restricts this
drug to use by or on the order
of a licensed veterinarian.

30
FLAVORED
TABLETS

Principal Display Panel - Galliprant 100 mg 90 Tablets Carton Label

GalliprantTM
(grapiprant tablets)

100 mg

For oral use
in dogs only

EP4 Prostaglandin
Receptor Antagonist NSAID

Caution: Federal law restricts this
drug to use by or on the order of
a licensed veterinarian.

90
FLAVORED
TABLETS

Elanco

Principal Display Panel - Galliprant 100 mg 90 Tablets Bottle Label

GalliprantTM
(grapiprant tablets)

100 mg

For oral use in dogs only

EP4 Prostaglandin Receptor
Antagonist NSAID

Caution: Federal law
restricts this drug to use
by or on the order of a
licensed veterinarian.

90
FLAVORED
TABLETS